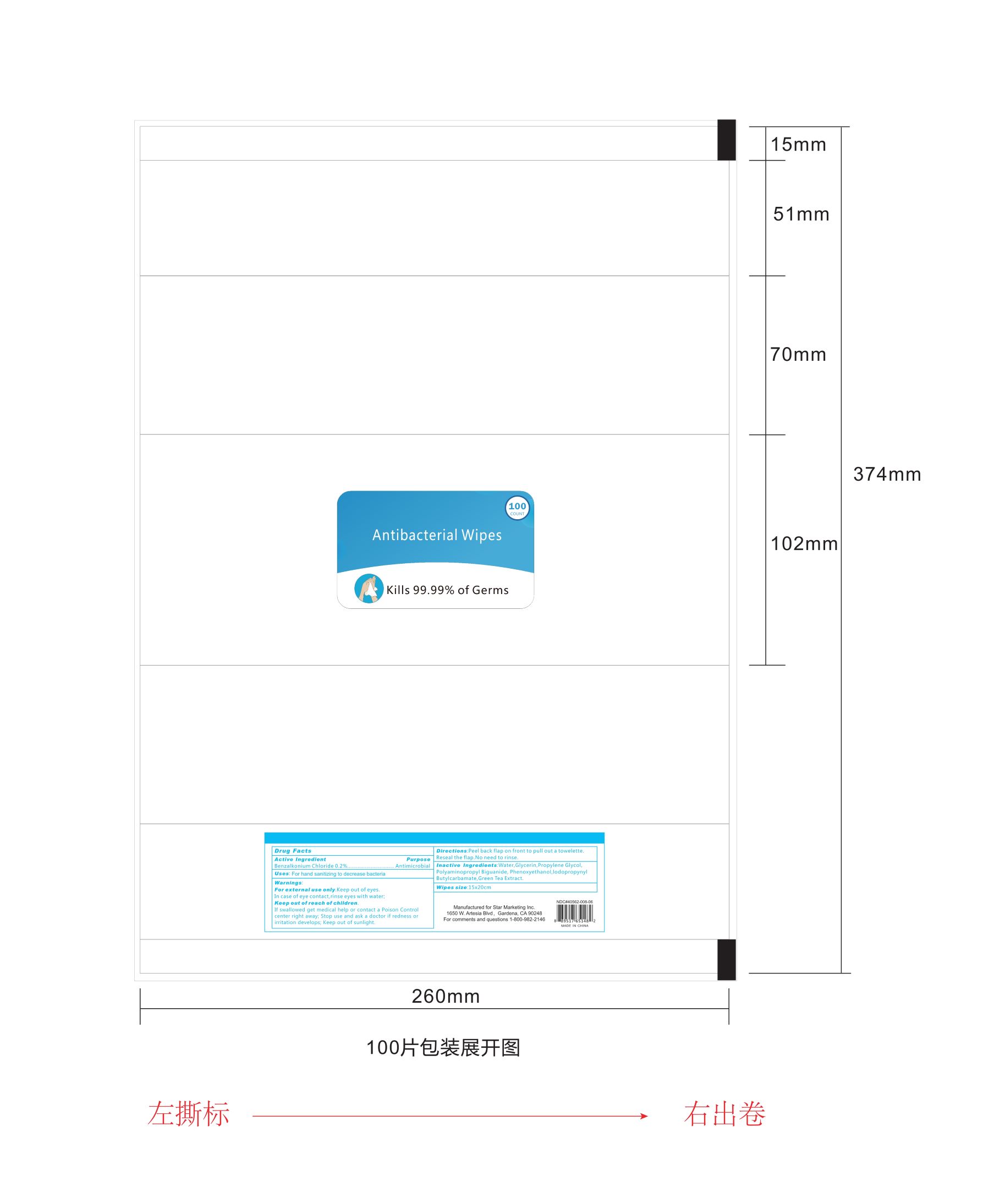 DRUG LABEL: Antibacterial Wipes
NDC: 40562-015 | Form: CLOTH
Manufacturer: Anhui Hanbon Daily Chemical Co., Ltd.
Category: otc | Type: HUMAN OTC DRUG LABEL
Date: 20200804

ACTIVE INGREDIENTS: BENZALKONIUM CHLORIDE 0.2 mg/100 mL
INACTIVE INGREDIENTS: IODOPROPYNYL BUTYLCARBAMATE; GREEN TEA LEAF; POLYAMINOPROPYL BIGUANIDE; PROPYLENE GLYCOL; GLYCERIN; PHENOXYETHANOL; WATER

Hanbon
Antibacterial Wipes
100PCS 40562-011-01

Active Ingredient(s)

Benzalkonium Chloride 0.2%

Purpose

Antimicrobial

Use

For hand sanitizing to decrease bacteria.

Warnings

For external use only.

Keep out of eyes. In case of eye contact, rinse eyes with water.

Keep out of sunlight.

WHEN USING

If eye contact occurs, rinse thoroughly with water.

Stop use and ask a doctor if rednes or irritation develops;

KEEP OUT OF REACH OF CHILDREN

If swallowed get medical help or contact a Poison Control center right away.

Directions

Peel back flap on front to pull out a towelette. Reseal the flap. No need to rinse.

Inactive ingredients

Water, Glycerin, Propylene Glycol, Polyaminopropyl Biguanide, Phenoxyethanol, Iodopropynyl Butylcarbamate, Green Tea Extract.

Package Label - Principal Display Panel

100 PATCH in 1 PACKET NDC: 40562-015-01